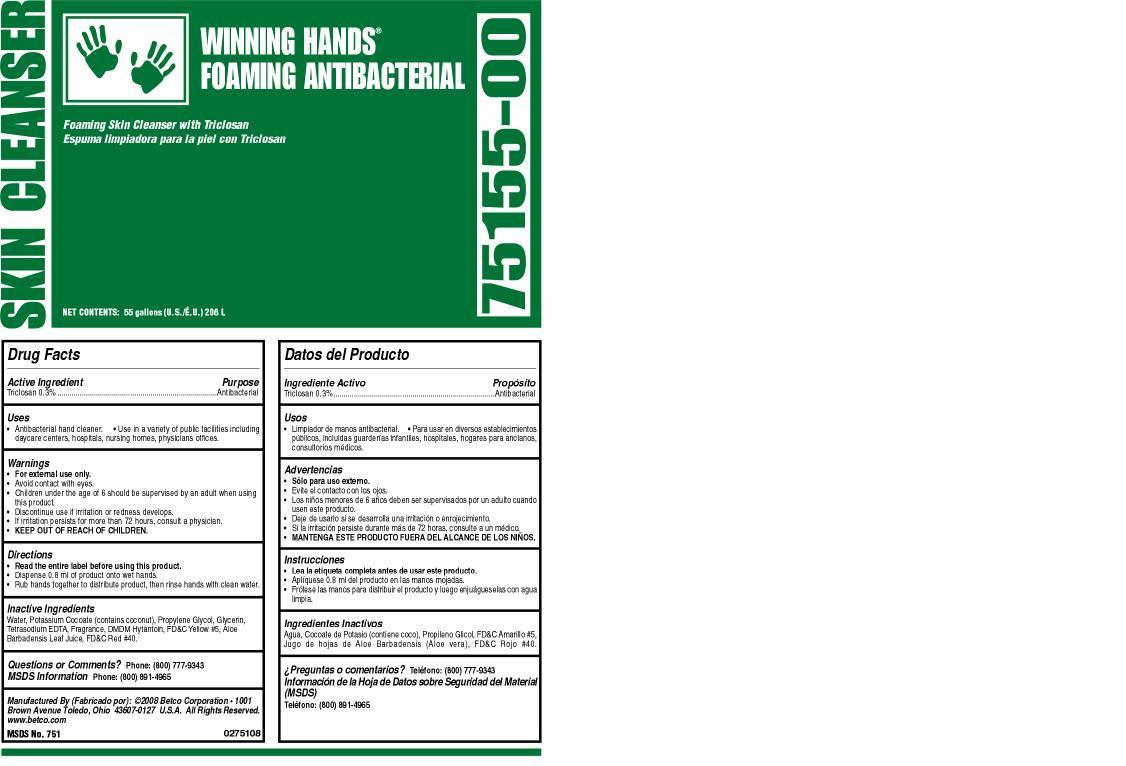 DRUG LABEL: Winning Hands Foaming Antibacterial
NDC: 65601-751 | Form: SOAP
Manufacturer: Betco Corporation, Ltd.
Category: otc | Type: HUMAN OTC DRUG LABEL
Date: 20121204

ACTIVE INGREDIENTS: TRICLOSAN 3.0 mg/1 mL
INACTIVE INGREDIENTS: WATER; POTASSIUM COCOATE; PROPYLENE GLYCOL; GLYCERIN; EDETATE SODIUM; DMDM HYDANTOIN; FD&C YELLOW NO. 5; ALOE VERA Leaf; FD&C RED NO. 40

Winning Hands Foaming Antibacterial

Winning Hands Foaming Antibacterial

Active Ingredient

Triclosan 0.30%

Winning Hands Foaming Antibacterial

Uses

- Antibacterial hand cleaner.
- Use in a variet of public facilities including daycare centers, hospitals, nursing homes, physicians offices.

Winning Hands Foaming Antibacterial

Warnings

- For external use only.
- Avoid contact with eyes.
- Children under the age of 6 should be supervised by an adult when using this product.
- Discontinue use is irritation or redness develops.
- If irritation persists for more than 72 hours, consult a physician.
- KEEP OUT OF REACH OF CHILDREN.

Winning Hands Foaming Antibacterial

Directions

- Read the entire label before using this product.
- Dispense 0.8 mL of product onto wet palm.
- Rub hands together to distribute product, then rinse hands with clean.

Winning Hands Foaming Antibacterial

Inactive Ingredients

Water, Potasium cocoate (contains coconut), Propylene Glycol, Glycerine, DMDM Hydantoin, Fragrance, FD&C Yellow #5, Aloe Barbadensis Leaf Juice. FD&C Red #40.

Winning Hands Foaming Antibacterial

Questions or Comments? Phone: (800) 777-9343

MDS information:(800) 891-4965

Winning Hands Foaming Antibacterial

Purpose

Antibacterial

Winning Hands Foaming Antibacterial

KEEP OUT OF REACH OF CHILDREN

Winning Hands Foaming Antibacterial

75155-00

Foaming Skin Cleanser with Triclosan

NET CONTENTS: 55 gallons (U.S./E.U.) 208 L